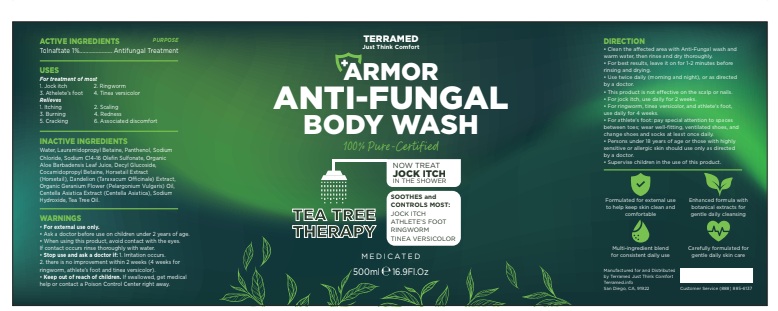 DRUG LABEL: Terramed Just Think Comfort Armor Anti Fungal Medicated Body Wash
NDC: 83004-032 | Form: GEL
Manufacturer: Rida LLC
Category: otc | Type: HUMAN OTC DRUG LABEL
Date: 20260204

ACTIVE INGREDIENTS: TOLNAFTATE 1 g/100 g
INACTIVE INGREDIENTS: TETRASODIUM GLUTAMATE DIACETATE; EUCALYPTUS OIL; WATER; SODIUM GLUCONATE; SODIUM PALM KERNELATE; GLYCERIN; MELALEUCA ALTERNIFOLIA LEAF; SODIUM CHLORIDE; ACTIVATED CHARCOAL; SODIUM COCOATE; SODIUM PALMATE; SODIUM LAURETH SULFATE

Active ingredient

Tolnaftate 1.0%

Purpose

Antifungal

Uses

For treatment of most

- jock itch
- ringworm
- atheletes foot
- tinea versicolor

Relieves

- itching
- scaling
- burning
- redness
- cracking
- associated discomfort

Warning

For external use only.

When using this product
When using this product avoid contact with the eye

Stop use and ask a doctor ifirritation occurs or if there is no
improvement within 2 weeks for jock itch or within 4 weeks for athlete's
foot and ringworm.

Do not use
Do Not use on children under 2 under of age except under the advice
and supervision of a doctor.

Keep out of reach of children. If swallowed, get medical help or contact a Poison Control Center right away.

Directions

- Make sure to dry affected area thoroughly.
- Supervise children in the use of this product.
- For Athlete's foot: pay special attention to the spaces between the toes; wear well-fitting, ventilated shoes and change shoes and socks at least once daily.
- Use 1-2 times daily. Use daily for 4 weeks; if condition persists longer, ask a doctor.
- This product is not effective on the scalp or nails.

Inactive ingredients

TETRASODIUM GLUTAMATE DIACETATE, EUCALYPTUS OIL, WATER, SODIUM GLUCONATE, SODIUM PALM KERNELATE, GLYCERIN, MELALEUCA ALTERNIFOLIA LEAF, SODIUM CHLORIDE, ACTIVATED CHARCOAL, SODIUM COCOATE, SODIUM PALMATE, SODIUM LAURETH SULFATE, SODIUM LAURYL SULFATE, SODIUM COCOATE